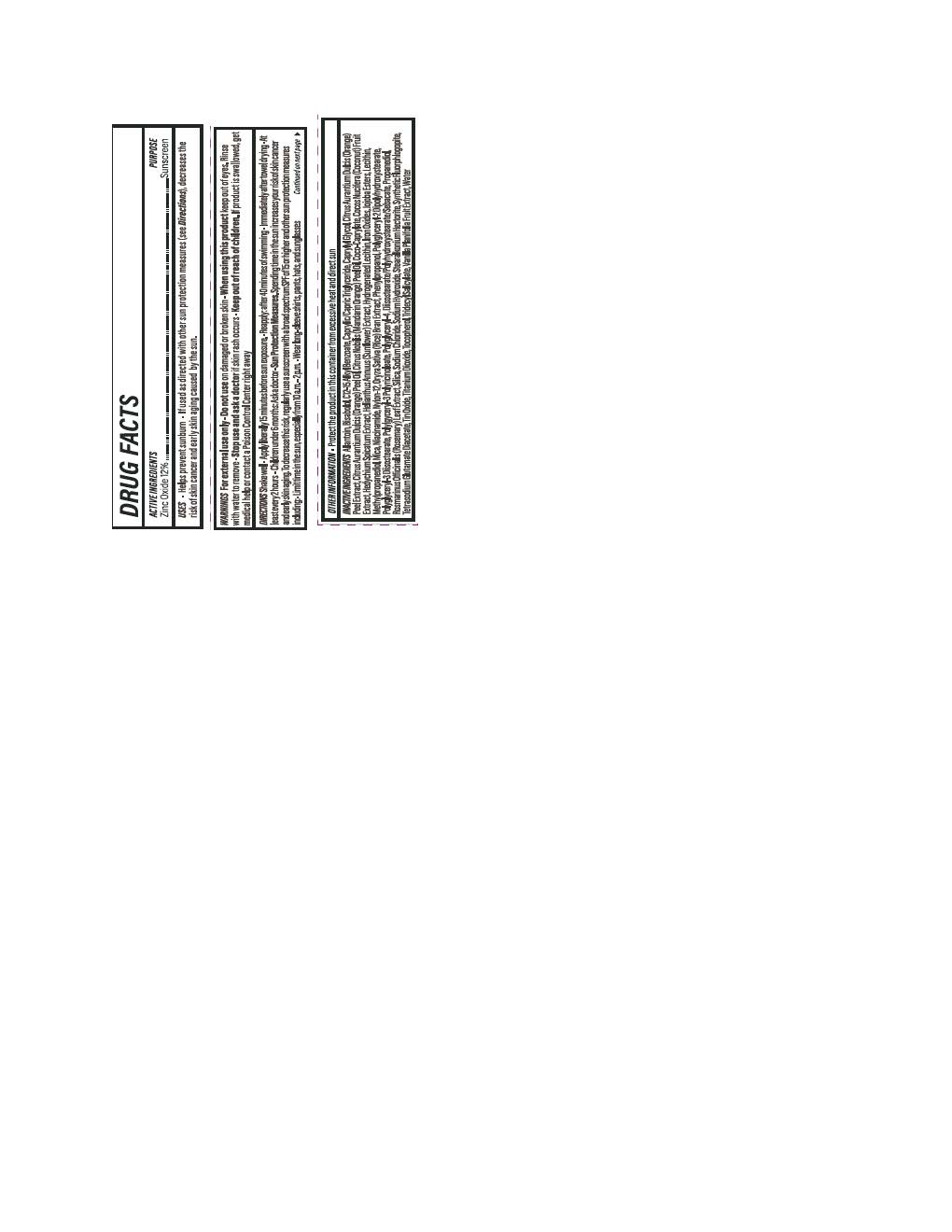 DRUG LABEL: Solarium Daily Essentials Luminizing Glow Drops
NDC: 84891-2191 | Form: LOTION
Manufacturer: Solarium Brands LLC
Category: otc | Type: HUMAN OTC DRUG LABEL
Date: 20251117

ACTIVE INGREDIENTS: ZINC OXIDE 132 mg/1 mL
INACTIVE INGREDIENTS: METHYLPROPANEDIOL; POLYGLYCERYL-2 DIPOLYHYDROXYSTEARATE; ALLANTOIN; ALKYL (C12-15) BENZOATE; ROSMARINUS OFFICINALIS FLOWER; .ALPHA.-BISABOLOL, (+)-; SODIUM HYDROXIDE; WATER; NIACINAMIDE; PROPANEDIOL; TETRASODIUM GLUTAMATE DIACETATE; SODIUM CHLORIDE; SILICON DIOXIDE; TOCOPHEROL; CAPRYLYL GLYCOL; COCO-CAPRYLATE; NYLON-12; PHENYLPROPANOL; HELIANTHUS ANNUUS FLOWERING TOP; LECITHIN, SOYBEAN; POLYGLYCERYL-4 DIISOSTEARATE/POLYHYDROXYSTEARATE/SEBACATE; POLYGLYCERYL-3 DIISOSTEARATE; STEARALKONIUM HECTORITE; CAPRYLIC/CAPRIC TRIGLYCERIDE; MICA; FERRIC OXIDE RED; CITRUS NOBILIS (MANDARIN ORANGE) PEEL OIL; HEDYCHIUM SPICATUM ROOT; CITRUS AURANTIUM DULCIS (ORANGE) PEEL OIL; TITANIUM DIOXIDE; FERRIC OXIDE YELLOW; FERROSOFERRIC OXIDE; TIN OXIDE; COCOS NUCIFERA (COCONUT) OIL; JOJOBA OIL; ORYZA SATIVA WHOLE; TRIDECYL SALICYLATE

Solarium Daily Essentials Luminizing Glow Drops